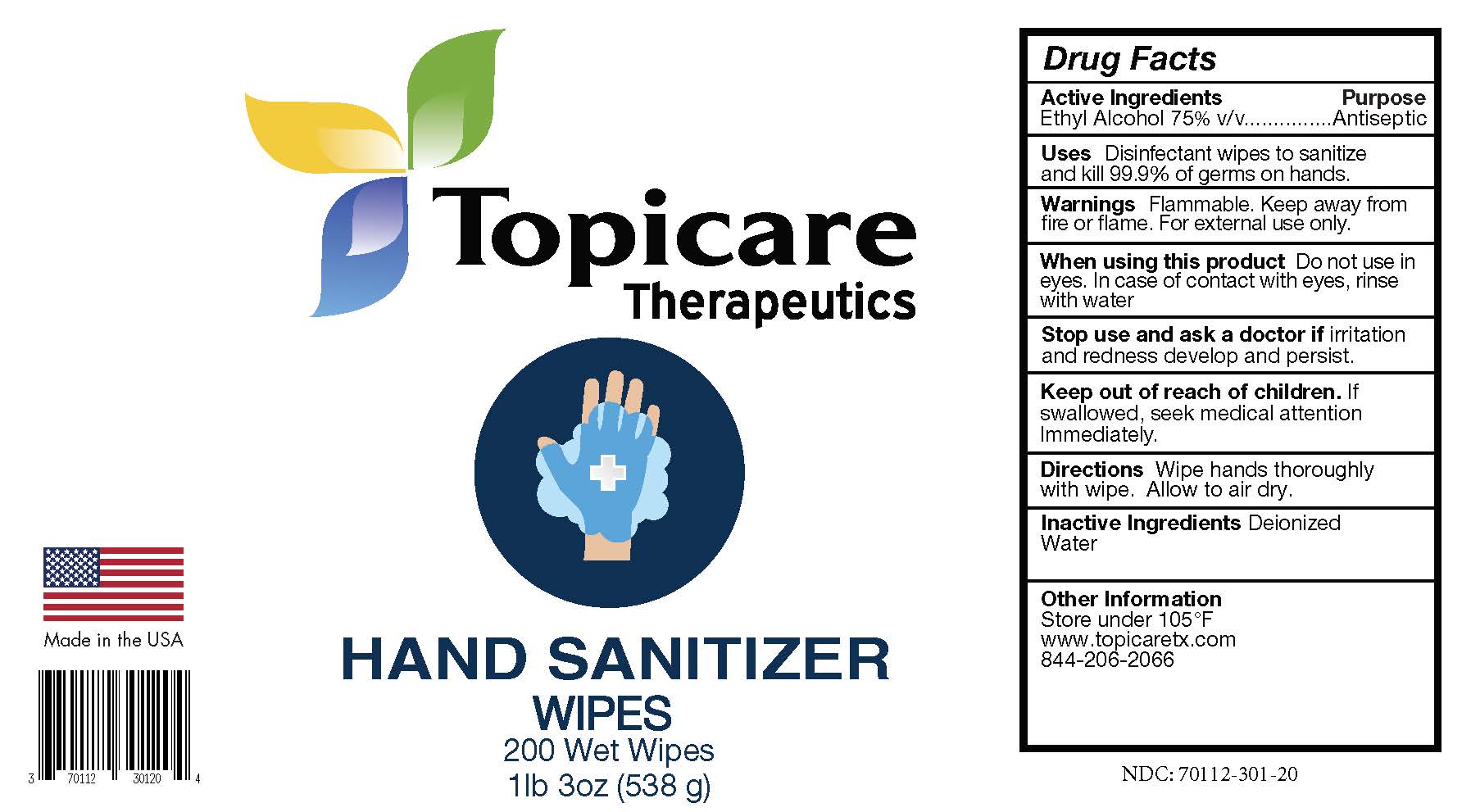 DRUG LABEL: Topicare Therapeutics Hand Sanitizer Wipes
NDC: 70112-301 | Form: CLOTH
Manufacturer: Topicare Management, LLC
Category: otc | Type: HUMAN OTC DRUG LABEL
Date: 20201105

ACTIVE INGREDIENTS: ALCOHOL 75 mL/100 mL
INACTIVE INGREDIENTS: WATER

Top Hand Wipes 200ct

Active Ingredient(s)

Ethyl Alcohol 75%

Purpose

Antiseptic

Use

Disinfectant wipes to sanitize and kill 99.9% of germs on hands.

Warnings

Flammable. Keep away from heat or flame. For external use only.

Do not use on children less than 2 months of age.

On open skin wounds.

In or near the eyes.

When Using

When using this product keep out of eyes, ear and mouth. In case of contact with eyes, rinse eyes thoroughly with water.

Keep Out of Reach of Children

If swallowed, get medical help or contact a Poison Control Center right away.

Directions

Wipe hands thoroughly with wipe. Allow to air dry.

Other Information

Store between 15-30°C (59-86°F)

Avoid freezing and excessive heat above 40°C (104°F)

Dispose of used wipe in trash; do not flush down toilet.

Inactive Ingredients

Deionized Water

Package Label

1lb 3oz (538g)

NDC: 70112-301-20